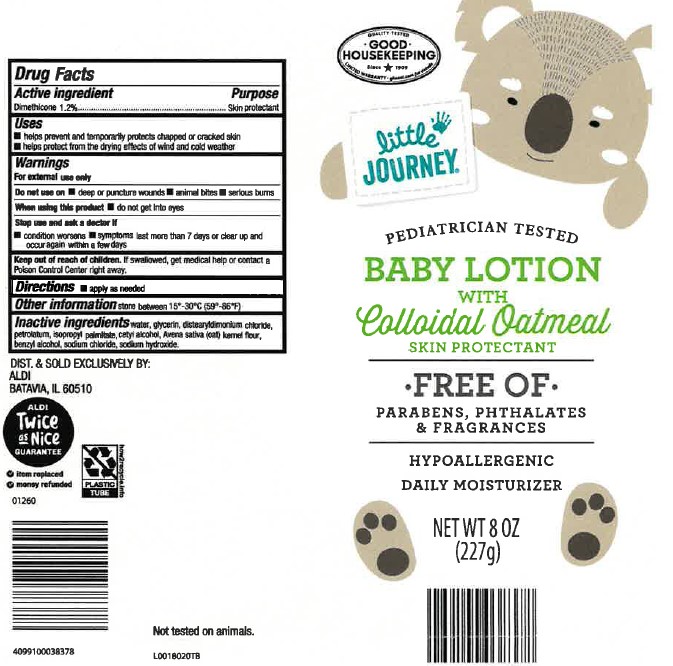 DRUG LABEL: DAILY MOISTURIZING
NDC: 64024-496 | Form: LOTION
Manufacturer: Aldi, Inc
Category: otc | Type: HUMAN OTC DRUG LABEL
Date: 20260129

ACTIVE INGREDIENTS: DIMETHICONE, UNSPECIFIED 12 mg/1 g
INACTIVE INGREDIENTS: WATER; GLYCERIN; DISTEARYLDIMONIUM CHLORIDE; PETROLATUM; ISOPROPYL PALMITATE; CETYL ALCOHOL; OATMEAL; BENZYL ALCOHOL; SODIUM CHLORIDE; SODIUM HYDROXIDE

Little Journey 496.000/496AA
Daily Baby Lotion with Colloidal Oatmeal

ACTIVE INGREDIENT

Dimethicone 1.2%

PURPOSE

Skin protectant

Uses

- helps prevent and temporarily protects chapped or cracked skin
- helps protect from the drying effects of wind and cold weather

Warnings

for this product

Do not use on

- deep or puncture wounds
- animal bites
- serious burns

When using this product

- do not get into eyes

Stop use and ask a doctor if

- condition worsens
- symptoms last more than 7 days or clear up and occur again within a few days

Keep out of reach of children.

If swallowed, get medical help or contact a Poison Control Center right away.

Directions

- apply as needed

Other information

store between 15 - 30C (59 - 86F)

Inactive ingredients

water, glycerin, distearyldimonium chloride, petrolatum, isopropyl palmitate, cetyl alcohol, Avena sativa (oat) kernel flour, benzyl alcohol, sodium chloride, sodium hydroxide

ADVERSE REACTION

DIST. & SOLD EXCLUSIVELY BY:

ALDI

BATAVIA, IL 60510

ALDI TWICE AS NICE GUARANTEE

- item replaced
- money refunded

PLASTIC TUBE

how2recycle.info

Not tested on animals.

PRINCIPAL DISPLAY PANEL

QUALITY TESTED

GOOD HOUSEKEEPING

since 1909

little JOURNEY®

PEDIATRICIAN TESTED

BABY LOTION

WITH

COLLOIDAL OATMEAL

SKIN PROTECTANT

FREE OF

PARABENS, PHTHALATES & FRAGRANCES

HYPOALLERGENIC

DAILY MOISTURIZER

NET WT 8 OZ (227 g)